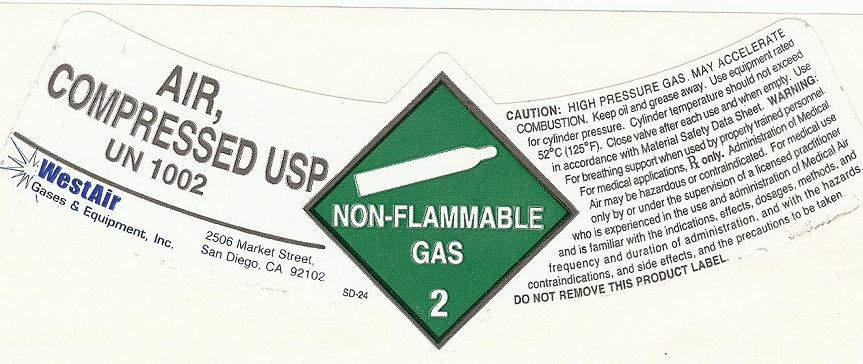 DRUG LABEL: Air
                
NDC: 53440-005 | Form: GAS
Manufacturer: WestAir Gases & Equipment, Inc. 
Category: prescription | Type: HUMAN PRESCRIPTION DRUG LABEL
Date: 20121009

ACTIVE INGREDIENTS: Air 995 mL/1 L

Air

PACKAGE LABEL

AIR
COMPRESSED USP
UN 1002
WestAir 2506 Market Street
Gases and Equipment, Inc. San Diego, Ca 92102
NON-FLAMMABLE
GAS
2
CAUTION: HIGH PRESSURE GAS, MAY ACCELERATE
COMBUSTION. Keep oil and grease away. Use equipment rated
for cylinder pressure. Cylinder temperature should not exceed
52 degrees C (125 degrees F). Clos3e valve after each use and when empty. Use
in accordance with Material Safety Data Sheet. WARNING:
For breathing support when used by properly trained personnel.
For medical applications, Rx only. Administration of Medical
Air may be hazardous of contraindicated. For medical use
only by or under the supervision of a licensed practitioner
who is experianced in the use and administration of Medical Air
and is familiar with the indications, effects, dosages, methods, and
frequency and duration of administration, and with the hazards,
contraindications, and side effects, and the precautions to be taken.
DO NOT REMOVE THIS PRODUCT LABEL